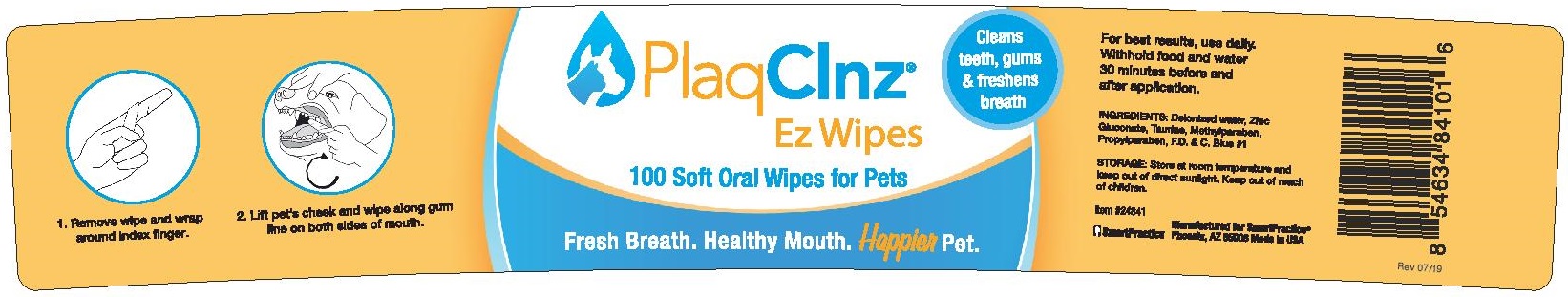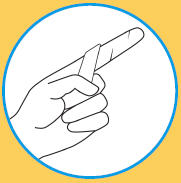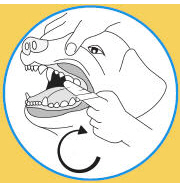 DRUG LABEL: PlaqClnz Ez Wipes
NDC: 69521-005 | Form: SOLUTION
Manufacturer: SmartHeatlh, Inc. (DBA SmartPractice)
Category: animal | Type: OTC ANIMAL DRUG LABEL
Date: 20251219

ACTIVE INGREDIENTS: Zinc Gluconate 0.0165 g/1 1
INACTIVE INGREDIENTS: WATER; TAURINE; METHYLPARABEN; PROPYLPARABEN; FD&C BLUE NO. 1

PlaqClnz® Ez Wipes

DOSAGE AND ADMINISTRATION

1. Remove wipe and wrap around index finger

2. Lift pet's cheek and wipe along gum line on both sides of mouth.

For best results, use daily. Withhold food and water 30 minutes before and after application.

DESCRIPTION

INGREDIENTS: Deionized water, Zinc Gluconate, Taurine, Methylparaben, Propylparaben, F.D. & C. Blue #1

STORAGE AND HANDLING

STORAGE: Store at room temperature and keep out of direct sunlight. Keep out of reach of children.

PACKAGE LABEL

PlaqClnz®

Ez Wipes

Cleans
teeth, gums
& freshens
breath

100 Soft Oral wipes for pets

Fresh Breath. Healthy Mouth. Happier pet.

1. Remove wipe and wrap around index finger
2. Lift pet's cheek and wipe along gum line on both sides of mouth.

For best results, use daily. Withhold food and water 30 minutes before and after application.

INGREDIENTS: Deionized water, Zinc Gluconate, Taurine, Methylparaben, Propylparaben, F.D. & C. Blue #1

STORAGE: Store at room temperature and keep out of direct sunlight. Keep out of reach of children.

Item #24841

SmartPractice

Manufactured for SmartPractice®
Phoenix, AZ 85008 Made in USA